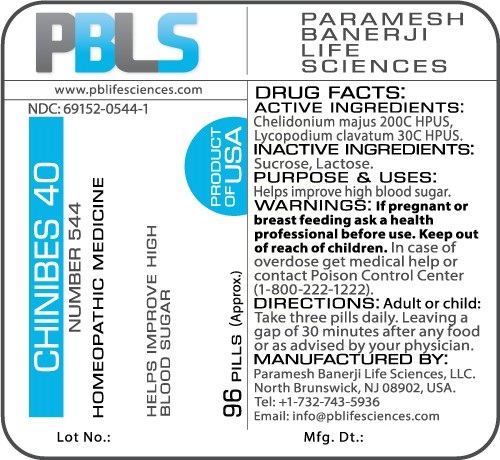 DRUG LABEL: Chinibes 40 (Number 544)
NDC: 69152-0544 | Form: PELLET
Manufacturer: Paramesh Banerji Life Sciences LLC
Category: homeopathic | Type: HUMAN OTC DRUG LABEL
Date: 20161111

ACTIVE INGREDIENTS: LYCOPODIUM CLAVATUM SPORE 30 [hp_C]/1 1; CHELIDONIUM MAJUS 200 [hp_C]/1 1
INACTIVE INGREDIENTS: SUCROSE; LACTOSE

DRUG FACTS: Active Ingredients

Chelidonium majus 200C HPUS, Lycopodium clavatum 30C HPUS

Inactive Ingredients

Sucrose, Lactose

Purpose

Helps improve high blood sugar

Uses

Helps improve high blood sugar

Warnings

If pregnant or breast feeding ask a health professional before use.

Keep out of reach of children. In case of overdose, get medical help or contact a Poison Control Center (1-800-222-1222) right away.

Direction

Adult or child: Take three pills daily. Leaving a gap of 30 minutes after any food or as advised by your physician.

Manufactured by

Paramesh Banerji Life Sciences, LLC.

North Brunswick, NJ 08902, USA.

Tel: +1-732-743-5936

Email: info@pblifesciences.com

Principal Display Panel

NDC: 69152-0544-1

Chinibes 40

Number 544

Homeopathic Medicine

Chelidonium majus 200C HPUS, Lycopodium clavatum 30C HPUS

Helps improve high blood sugar

96 Pills (Approx.)

Product of USA